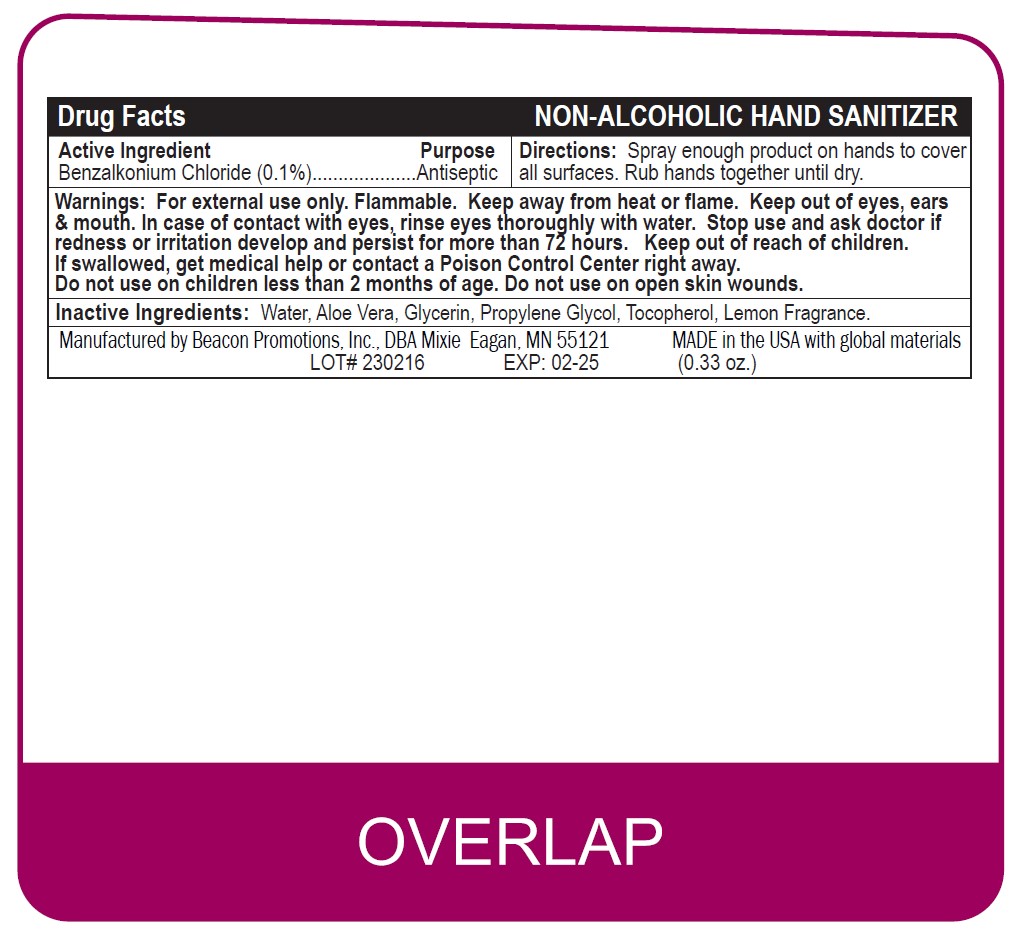 DRUG LABEL: SANSPRAY-NA
NDC: 70445-606 | Form: SPRAY
Manufacturer: Beacon Promotions, Inc.
Category: otc | Type: HUMAN OTC DRUG LABEL
Date: 20241231

ACTIVE INGREDIENTS: BENZALKONIUM CHLORIDE 1 mg/100 mL
INACTIVE INGREDIENTS: .ALPHA.-TOCOPHEROL ACETATE; ALOE; PROPYLENE GLYCOL; WATER; GLYCERIN

Hand Sanitizer Spray

Purpose

Antiseptic

Warnings:

For external use only. Flammable. Keep away from heat or flame. Keep out of eyes, ears
& mouth. In case of contact with eyes, rinse eyes thoroughly with water. Stop use and ask doctor if
redness or irritation develop and persist for more than 72 hours. Keep out of reach of children.
If swallowed, get medical help or contact a Poison Control Center right away.
Do not use on children less than 2 months of age. Do not use on open skin wounds.

Directions

Spray enough product on hands to cover
all surfaces. Rub hands together until dry.

Inactive Ingredient:

Water, Aloe Vera, Glycerin, Propylene Glycol, Tocopherol, Lemon Fragrance.

Purpose

Anticeptic

Drug Facts

Active Ingredient Purpose
Benzalkonium Chloride (0.1%)

Spray enough product on hands to cover
all surfaces. Rub hands together until dry.

Keep out of reach of children